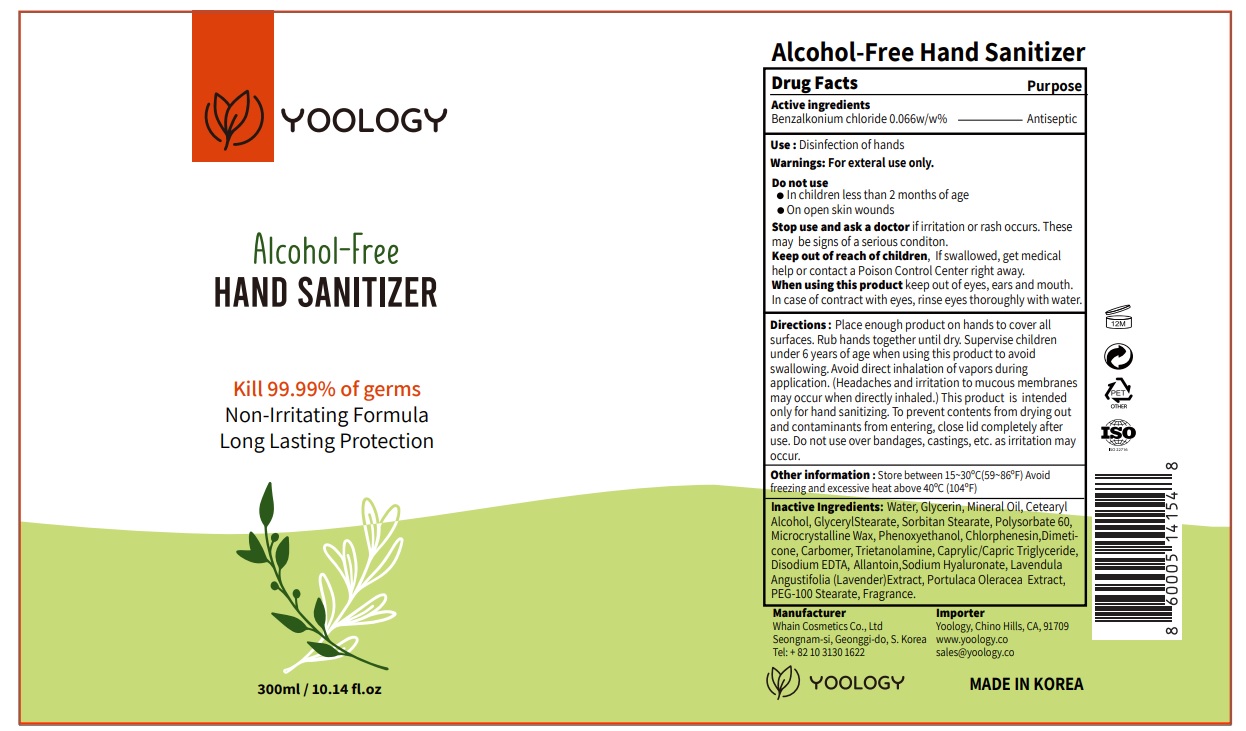 DRUG LABEL: YOOLOGY Alcohol-Free HAND SANITIZER
NDC: 73823-301 | Form: CREAM
Manufacturer: WHAIN COSMETIC
Category: otc | Type: HUMAN OTC DRUG LABEL
Date: 20210713

ACTIVE INGREDIENTS: BENZALKONIUM CHLORIDE 0.198 g/300 mL
INACTIVE INGREDIENTS: CETOSTEARYL ALCOHOL; GLYCERYL MONOSTEARATE; SORBITAN MONOSTEARATE; PHENOXYETHANOL; CHLORPHENESIN; MEDIUM-CHAIN TRIGLYCERIDES; PURSLANE; MICROCRYSTALLINE WAX; LAVANDULA ANGUSTIFOLIA SUBSP. ANGUSTIFOLIA FLOWERING TOP; GLYCERIN; DIMETHICONE; WATER; MINERAL OIL; EDETATE DISODIUM; ALLANTOIN; HYALURONATE SODIUM; PEG-100 STEARATE; POLYSORBATE 60; CARBOMER HOMOPOLYMER, UNSPECIFIED TYPE; TROLAMINE

[WHAIN COSMETIC] [300 mL, Bottle+Pump] YOOLOGY Alcohol-Free HAND SANITIZER

Active ingredient

Benzalkonium chloride 0.066w/w%

Directions

Place enough product on hands to cover all surfaces. Rub hands together until dry. Supervise children under 6 years of age when using this product to avoid swallowing. Avoid direct inhalation of vapors during application. (Headaches and irritation to mucous membranes may occur when directly inhaled.) This product is intended only for hand sanitizing. To prevent contents from drying out and contaminants from entering, close lid completely after use. Do not use over bandages, castings, etc. as irritation may occur.

Warnings

For exteral use only.

Stop use and ask a doctor

if irritation or rash occurs. These may be signs of a serious conditon.

Do not use

- In children less than 2 months of age
- On open skin wounds

Keep out of reach of children

If swallowed, get medical help or contact a Poison Control Center right away.

When using this product

keep out of eyes, ears and mouth. In case of contract with eyes, rinse eyes thoroughly with water.

Use

Disinfection of hands

Other information

Store between 15~30ºC(59~86ºF) Avoid freezing and excessive heat above 40ºC (104ºF)

Inactive Ingredients

Water, Glycerin, Mineral Oil, Cetearyl Alcohol, GlycerylStearate, Sorbitan Stearate, Polysorbate 60, Microcrystalline Wax, Phenoxyethanol, Chlorphenesin,Dimeticone, Carbomer, Trietanolamine, Caprylic/Capric Triglyceride, Disodium EDTA, Allantoin,Sodium Hyaluronate, Lavendula Angustifolia (Lavender)Extract, Portulaca Oleracea Extract, PEG-100 Stearate, Fragrance

Purpose

Antiseptic